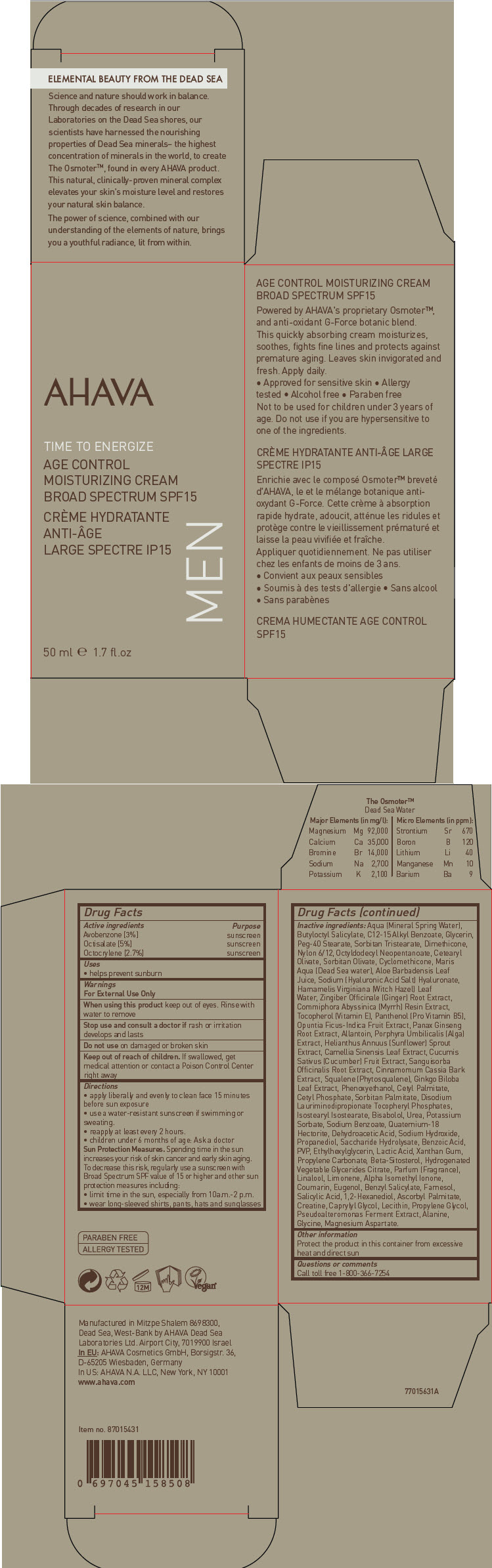 DRUG LABEL: AHAVA ACTIVE DEADSEA MINERALS 
NDC: 60289-282 | Form: CREAM
Manufacturer: AHAVA Dead Sea Laboratories Ltd
Category: otc | Type: HUMAN OTC DRUG LABEL
Date: 20231107

ACTIVE INGREDIENTS: Avobenzone 30 mg/1 mL; Octisalate 50 mg/1 mL; Octocrylene 27 mg/1 mL
INACTIVE INGREDIENTS: Water; Alkyl (C12-15) Benzoate; Butyloctyl Salicylate; Glycerin; Peg-40 Stearate; Sorbitan Tristearate; Octyldodecyl Neopentanoate; Dimethicone; Sorbitan Olivate; Cetearyl Olivate; Cyclomethicone; Phenoxyethanol; Cetyl Palmitate; Sorbitan Monopalmitate; Propylene Carbonate; Quaternium-18 Hectorite; Ethylhexylglycerin; Caprylyl Glycol; Hyaluronate Sodium; Aloe Vera Leaf; Cetyl Phosphate; Isostearyl Isostearate; Cucumber; Alanine; Creatine; Glycine; Magnesium Aspartate; Invert Sugar; Urea; Disodium Lauriminodipropionate Tocopheryl Phosphates; Propanediol; Chinese Cinnamon; Sanguisorba Officinalis Root; Levomenol; Xanthan Gum; Allantoin; Ginger; Ginkgo; Green Tea Leaf; Asian Ginseng; Panthenol; Hamamelis Virginiana Top Water; Ascorbyl Palmitate; .Beta.-Sitosterol; Propylene Glycol; Squalene; Tocopherol; Porphyra Umbilicalis; Prickly Pear Fruit; Helianthus Annuus Sprout; Salicylic Acid; Commiphora Madagascariensis Resin; Isomethyl-.Alpha.-Ionone; Benzyl Salicylate; Coumarin; Eugenol; Linalool, (+/-)-; Povidone K30; POTASSIUM SORBATE; SODIUM BENZOATE; SODIUM DEHYDROACETATE; SODIUM HYDROXIDE; LIMONENE, (-)-; FARNESOL, (2E,6Z)-; 1,2-HEXANEDIOL; Lecithin, Soybean

AHAVA ACTIVE DEADSEA MINERALS
TIME TO ENERGIZE AGE CONTROL MOISTURIZING BROAD SPECTRUM SPF15

Drug Facts

ACTIVE INGREDIENT

Active ingredients | Purpose
Avobenzone [3%] | sunscreen
Octisalate [5%] | sunscreen
Octocrylene [2.7%] | sunscreen

Uses

- helps prevent sunburn

Warnings

For External Use Only

When using this product keep out of eyes. Rinse with water to remove

Stop use and consult a doctor if rash or irritation develops and lasts

Do not use on damaged or broken skin

Keep out of reach of children. If swallowed, get medical attention or contact a Poison Control Center right away

Directions

- apply liberally and evenly to clean face 15 minutes before sun exposure
- use a water-resistant sunscreen if swimming or sweating.
- reapply at least every 2 hours.
- children under 6 months of age: Ask a doctor

Sun Protection Measures

Spending time in the sun increases your risk of skin cancer and early skin aging. To decrease this risk, regularly use a sunscreen with Broad Spectrum SPF value of 15 or higher and other sun protection measures including:

- limit time in the sun, especially from 10a.m.-2 p.m.
- wear long-sleeved shirts, pants, hats and sunglasses

Inactive ingredients

Aqua (Mineral Spring Water), Butyloctyl Salicylate, C12-15 Alkyl Benzoate, Glycerin, Peg-40 Stearate, Sorbitan Tristearate, Dimethicone, Nylon 6/12, Octyldodecyl Neopentanoate, Cetearyl Olivate, Sorbitan Olivate, Cyclomethicone, Maris Aqua (Dead Sea water), Aloe Barbadensis Leaf Juice, Sodium (Hyaluronic Acid Salt) Hyaluronate, Hamamelis Virginiana (Witch Hazel) Leaf Water, Zingiber Officinale (Ginger) Root Extract, Commiphora Abyssinica (Myrrh) Resin Extract, Tocopherol (Vitamin E), Panthenol (Pro Vitamin B5), Opuntia Ficus-Indica Fruit Extract, Panax Ginseng Root Extract, Allantoin, Porphyra Umbilicalis (Alga) Extract, Helianthus Annuus (Sunflower) Sprout Extract, Camellia Sinensis Leaf Extract, Cucumis Sativus (Cucumber) Fruit Extract, Sanguisorba Officinalis Root Extract, Cinnamomum Cassia Bark Extract, Squalene (Phytosqualene), Ginkgo Biloba Leaf Extract, Phenoxyethanol, Cetyl Palmitate, Cetyl Phosphate, Sorbitan Palmitate, Disodium Lauriminodipropionate Tocopheryl Phosphates, Isostearyl Isostearate, Bisabolol, Urea, Potassium Sorbate, Sodium Benzoate, Quaternium-18 Hectorite, Dehydroacetic Acid, Sodium Hydroxide, Propanediol, Saccharide Hydrolysate, Benzoic Acid, PVP, Ethylhexylglycerin, Lactic Acid, Xanthan Gum, Propylene Carbonate, Beta-Sitosterol, Hydrogenated Vegetable Glycerides Citrate, Parfum (Fragrance), Linalool, Limonene, Alpha Isomethyl Ionone, Coumarin, Eugenol, Benzyl Salicylate, Farnesol, Salicylic Acid, 1,2-Hexanediol, Ascorbyl Palmitate, Creatine, Caprylyl Glycol, Lecithin, Propylene Glycol, Pseudoalteromonas Ferment Extract, Alanine, Glycine, Magnesium Aspartate.

Other information

Protect the product in this container from excessive heat and direct sun

Questions or comments

Call toll free 1-800-366-7254

PRINCIPAL DISPLAY PANEL - 50 ml Bottle Carton

AHAVA

TIME TO ENERGIZE

AGE CONTROL
MOISTURIZING CREAM
BROAD SPECTRUM SPF15

MEN

50 ml e 1.7 fl.oz